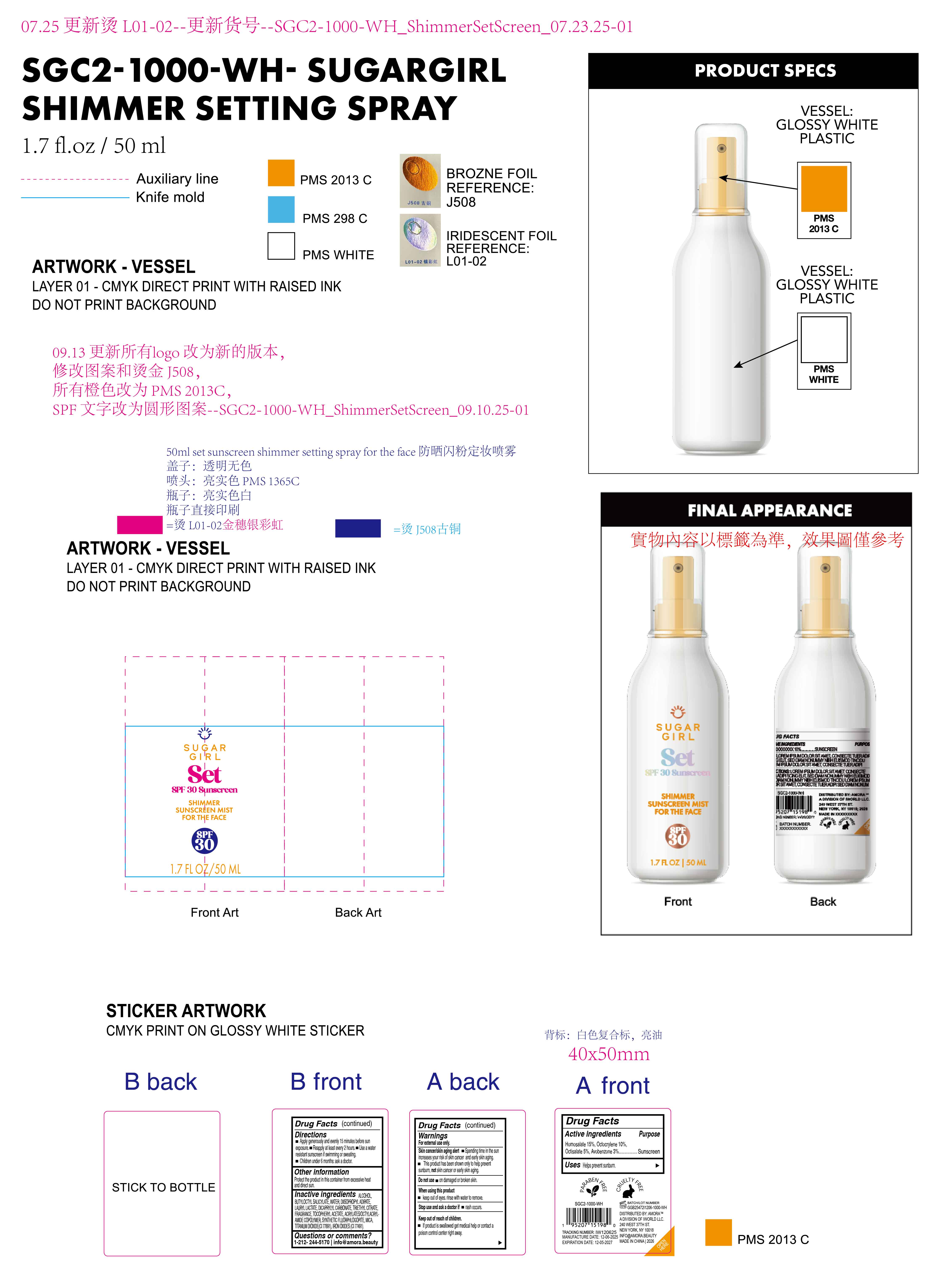 DRUG LABEL: Sugargirl Set SPF 30 sunscreen shimmer sunscreen mist for the face
NDC: 85161-146 | Form: SPRAY
Manufacturer: Longway Technology(Guangzhou)Co.,Ltd.
Category: otc | Type: HUMAN OTC DRUG LABEL
Date: 20251204

ACTIVE INGREDIENTS: AVOBENZONE 0.03 g/1 mL; OCTISALATE 0.05 g/1 mL; OCTOCRYLENE 0.1 g/1 mL; HOMOSALATE 0.15 g/1 mL
INACTIVE INGREDIENTS: ACRYLATES/OCTYLACRYLAMIDE COPOLYMER (40000 MW); DICAPRYLYL CARBONATE; BUTYLOCTYL SALICYLATE; TRIETHYL CITRATE; ALCOHOL; CI 77491; MAGNESIUM POTASSIUM ALUMINOSILICATE FLUORIDE; CI 77891; MICA; ALPHA-TOCOPHEROL ACETATE; LAURYL LACTATE; DIISOPROPYL ADIPATE; FRAGRANCE 13576; WATER

ACTIVE INGREDIENT

Homosalate 15%, Octocrylene 10%, Octisalate 5% , Avobenzone 3%

INACTIVE INGREDIENT

ALCOHOL,BUTYLOCTYL SALICYLATE,WATER,DIISOPROPYL ADIPATE,LAURYL LACTATE,DICAPRYLYL CARBONATE,TRIETHYL CITRATE,FRAGRANCE,TOCOPHERYL ACETATE,ACRYLATES/OCTYLACRYLAMIDE COPOLYMER,SYNTHETIC FLUORPHLOGOPITE,MICA,TITANIUM DIOXIDE(CI 77891),IRON OXIDES (CI 77491)

PURPOSE

Sunscreen

KEEP OUT OF REACH OF CHILDREN

lf product is swallowed get medical help or contact a poison control center right away.

Directions

Apply generously and evenly 15 minutes before sun exposure.

Reapply at least every 2 hours.

Use a water resistant sunscreen if swimming or sweating.

Children under 6 months: ask a doctor.

INDICATIONS AND USAGE

Helps prevent sunburn

Warnings

For external use only.

Skin cancer/skin aging alert

Spending time in the sun increases your risk of skin cancer and early skin aging.

This product has been shown only to help prevent sunburn, not skin cancer or early skin aging.

Do not use on damaged or broken skin.

When using this product
keep out of eyes. rinse with water to remove.

Stop use and ask a doctorif rash occurs.

Keep out of reach of children.

lf product is swallowed get medical help or contact a poison control right away.

OTHER SAFETY INFORMATION

Protect the product in this container from excessive heat and direct sun.

QUESTIONS

1-212-244-5170 info@amora.beauty